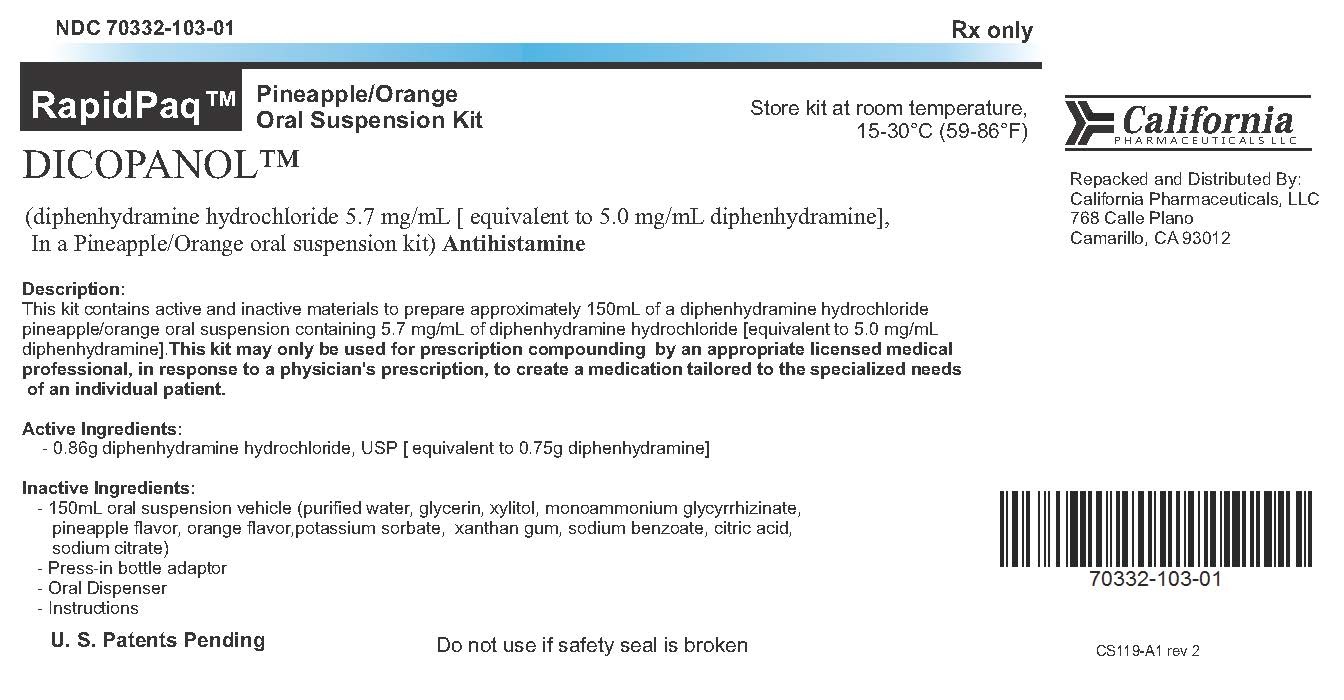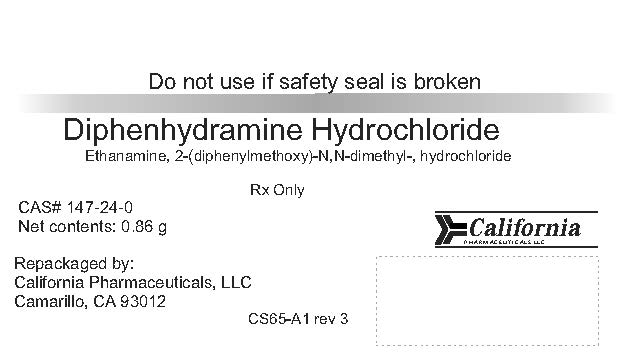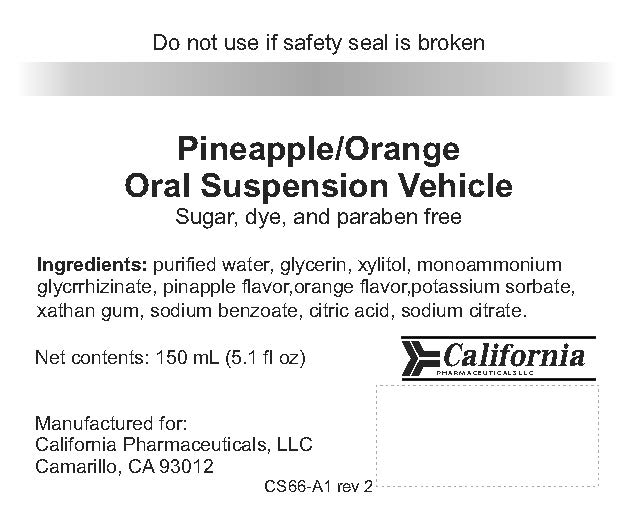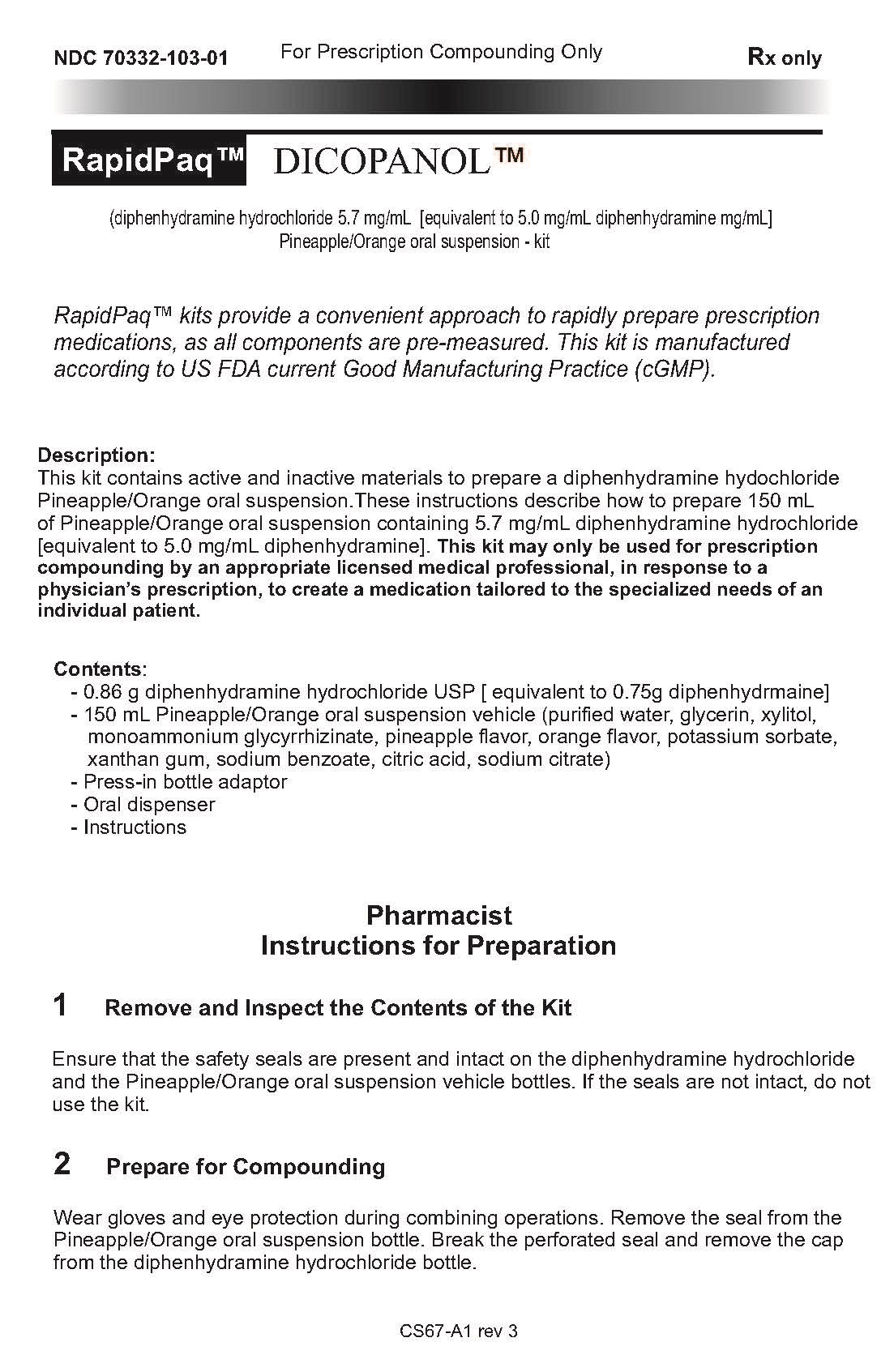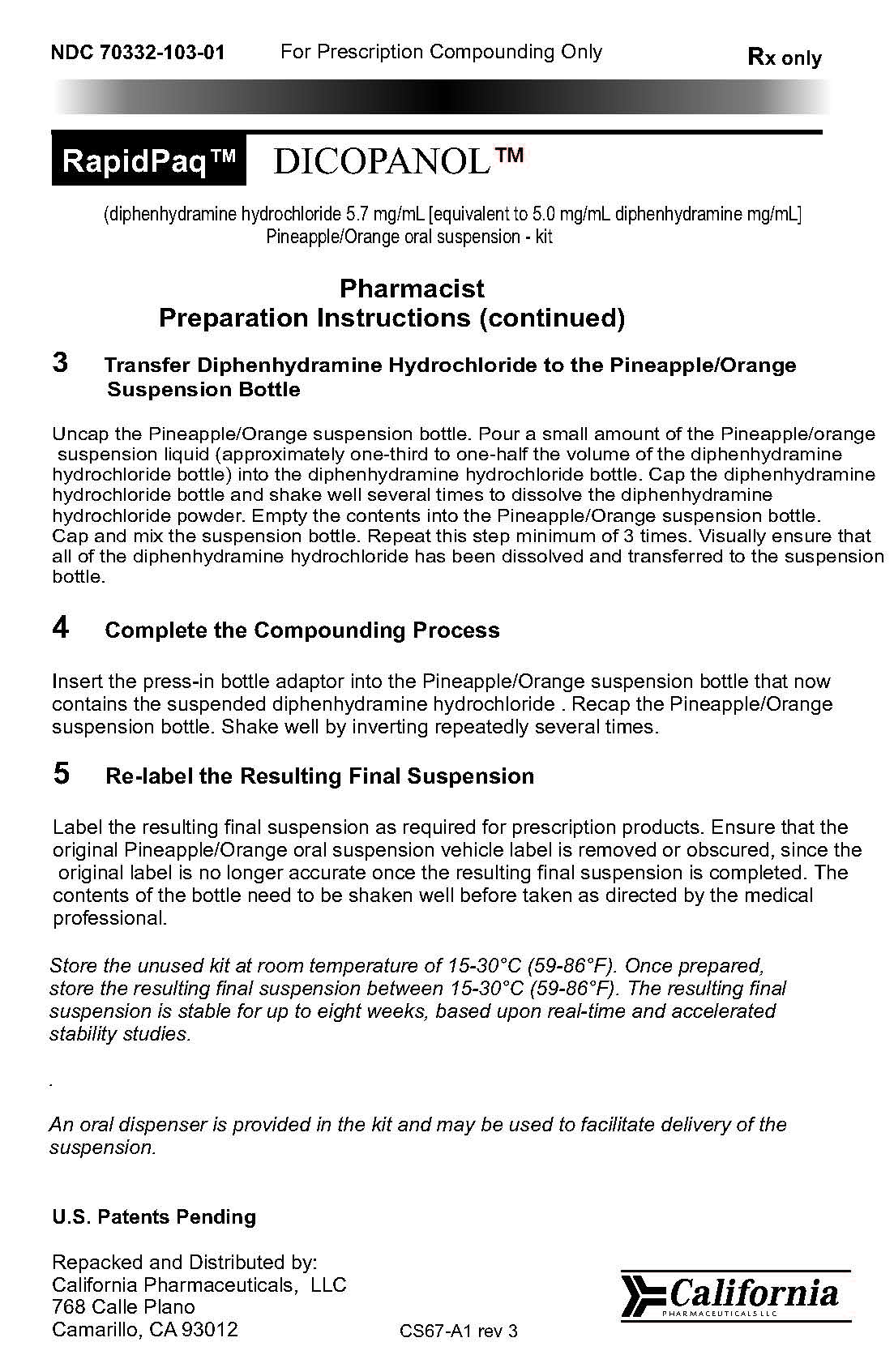 DRUG LABEL: Dicopanol
NDC: 70332-103 | Form: KIT | Route: ORAL
Manufacturer: California Pharmaceuticals LLC
Category: prescription | Type: HUMAN PRESCRIPTION DRUG LABEL
Date: 20160107

ACTIVE INGREDIENTS: DIPHENHYDRAMINE HYDROCHLORIDE 0.86 g/0.86 g
INACTIVE INGREDIENTS: SODIUM CITRATE; WATER; GLYCERIN; XYLITOL; GLYCYRRHIZIN, AMMONIATED; PINEAPPLE; XANTHAN GUM; SODIUM BENZOATE; ORANGE; CITRIC ACID MONOHYDRATE; MELATONIN; POTASSIUM SORBATE; STEVIA LEAF

Dicopanol